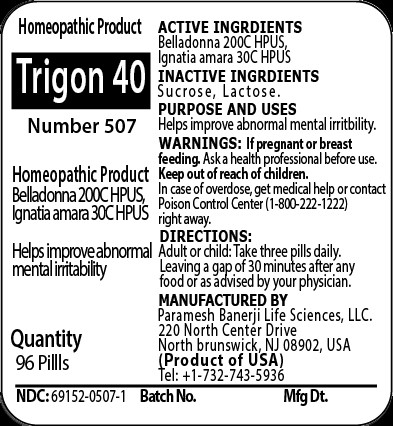 DRUG LABEL: Trigon 40 (Number 507)
NDC: 69152-0507 | Form: PELLET
Manufacturer: Paramesh Banerji Life Sciences LLC
Category: homeopathic | Type: HUMAN OTC DRUG LABEL
Date: 20150929

ACTIVE INGREDIENTS: ATROPA BELLADONNA 200 [hp_C]/1 1; STRYCHNOS IGNATII SEED 30 [hp_C]/1 1
INACTIVE INGREDIENTS: SUCROSE; LACTOSE

Active Ingredients

Belladonna 200C HPUS, Ignatia amara 30C HPUS

Inactive Ingredients

Sucrose, Lactose

Purpose

Helps improve abnormal mental irritability

Uses

Helps improve abnormal mental irritability

Warnings

If pregnant or breast feeding ask a health professional before use.

Keep out of reach of children. In case of overdose, get medical help or contact a Poison Control Center (1-800-222-1222) right away.

Direction

Adult or child: Take three pills daily. Leaving a gap of 30 minutes after any food or as advised by your physician.

Manufactured by

Paramesh Banerji Life Sciences, LLC

220 North Center Drive

North Brunswick, NJ 08902, USA

Product of USA

Tel: +1-732-743-5936

Principal Display Panel

Homeopathic Product

Trigon 40

Number 507

Homeopathic Product

Belladonna 200C, Ignatia amara 30C HPUS

Helps improve abnormal mental irritability

Quantity

96 Pills